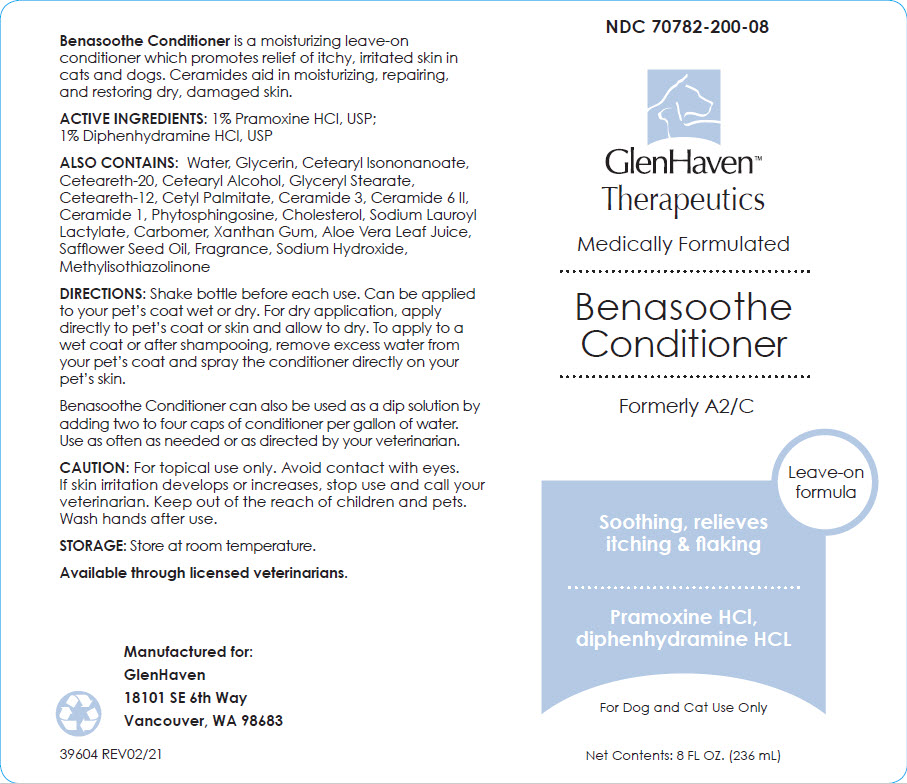 DRUG LABEL: Glen Haven Benasoothe Conditioner
NDC: 70782-200 | Form: SPRAY, SUSPENSION
Manufacturer: GlenHaven LLC
Category: animal | Type: OTC ANIMAL DRUG LABEL
Date: 20211208

ACTIVE INGREDIENTS: PRAMOXINE HYDROCHLORIDE 10 mg/1 mL; DIPHENHYDRAMINE HYDROCHLORIDE 10 mg/1 mL

Glen Haven™ Benasoothe Conditioner Spray

VETERINARY INDICATIONS

Benasoothe Conditioner is a moisturizing leave-on conditioner which promotes relief of itchy, irritated skin in cats and dogs. Ceramides aid in moisturizing, repairing, and restoring dry, damaged skin.

DESCRIPTION

ACTIVE INGREDIENTS: 1% Pramoxine HCl, USP; 1% Diphenhydramine HCl, USP

ALSO CONTAINS: Water, Glycerin, Cetearyl lsononanoate, Ceteareth-20, Cetearyl Alcohol, Glyceryl Stearate, Ceteareth-12, Cetyl Palmitate, Ceramide 3, Ceramide 6 II, Ceramide 1, Phytosphingosine, Cholesterol, Sodium Lauroyl Lactylate, Carbomer, Xanthan Gum, Aloe Vera Leaf Juice, Safflower Seed Oil, Fragrance, Sodium Hydroxide, Methylisothiazolinone

DOSAGE AND ADMINISTRATION

DIRECTIONS: Shake bottle before each use. Can be applied to your pet's coat wet or dry. For dry application, apply directly to pet's coat or skin and allow to dry. To apply to a wet coat or after shampooing, remove excess water from your pet's coat and spray the conditioner directly on your pet's skin.

Benasoothe Conditioner can also be used as a dip solution by adding two to four caps of conditioner per gallon of water. Use as often as needed or as directed by your veterinarian.

WARNINGS

CAUTION: For topical use only. Avoid contact with eyes. If skin irritation develops or increases, stop use and call your veterinarian. Keep out of the reach of children and pets. Wash hands after use.

HOW SUPPLIED

STORAGE: Store at room temperature.

Available through licensed veterinarians.

Manufactured for:
GlenHaven
18101 SE 6th Way
Vancouver, WA 98683

39604 REV02/21

PRINCIPAL DISPLAY PANEL - 236 mL Bottle Label

NDC 70782-200-08

GlenHaven™
Therapeutics

Medically Formulated

Benasoothe
Conditioner

Formerly A2/C

Leave-on
formula

Soothing, relieves
itching & flaking

Pramoxine HCl,
diphenhydramine HCL

For Dog and Cat Use Only

Net Contents: 8 FL OZ. (236 mL)